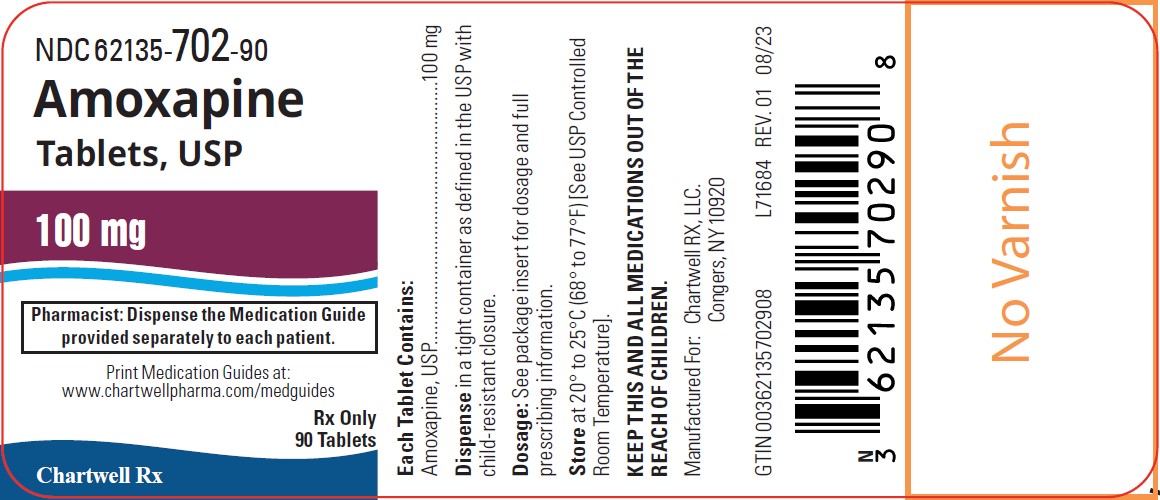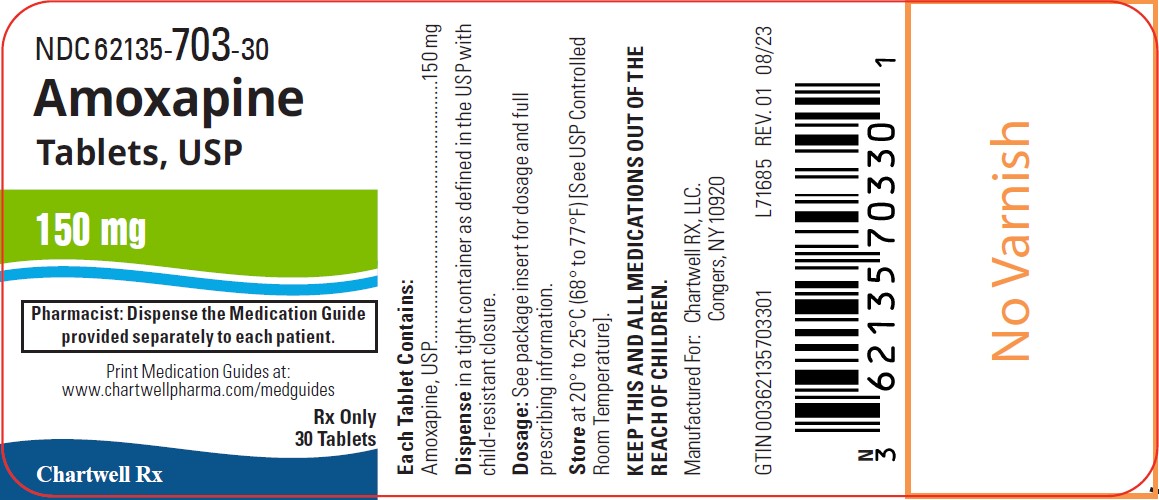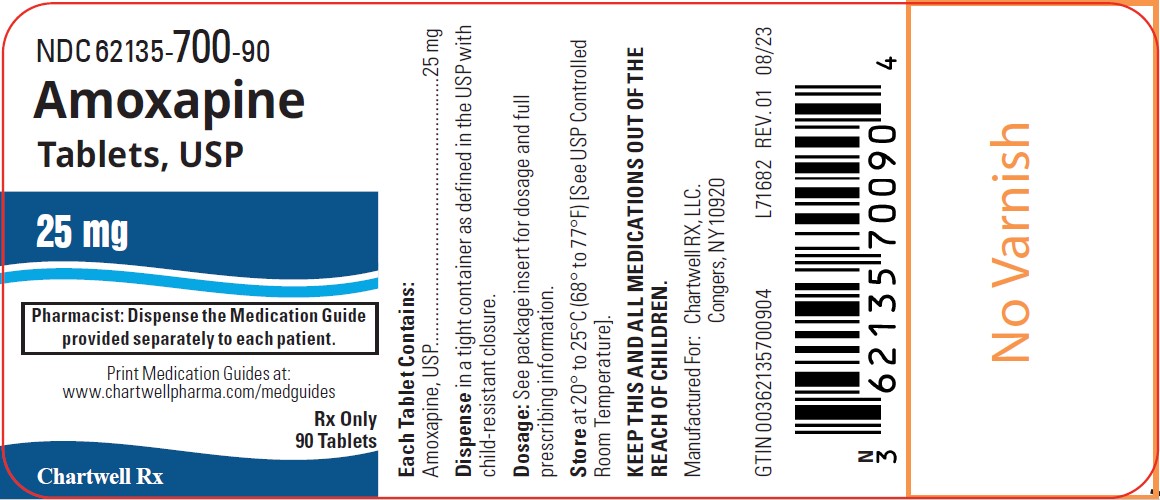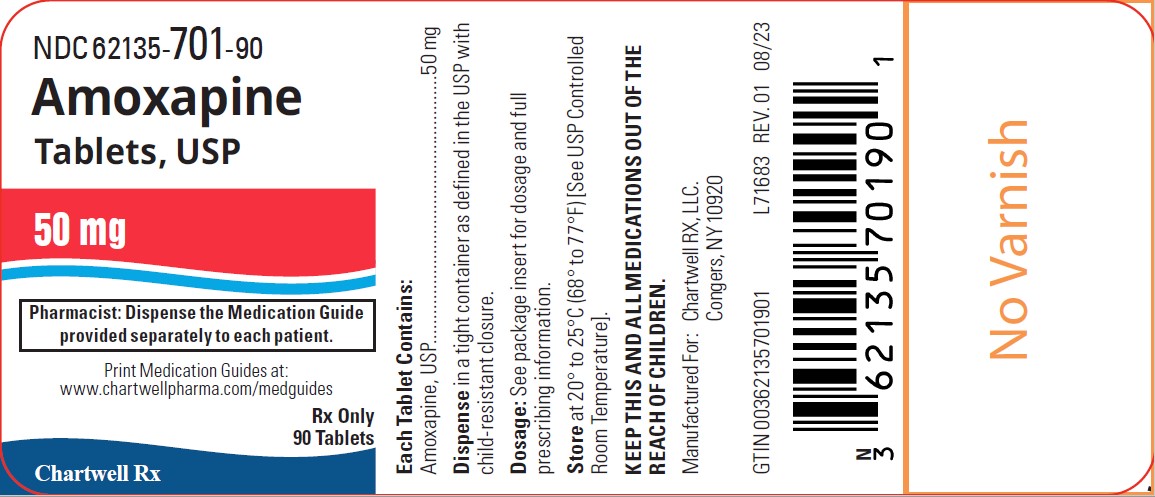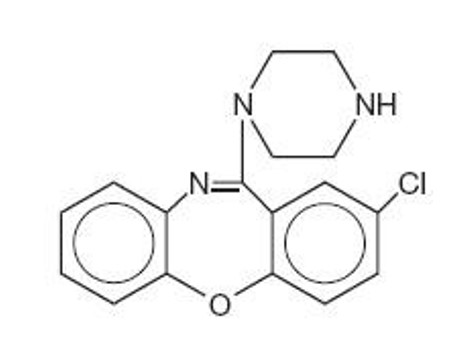 DRUG LABEL: Amoxapine
NDC: 62135-700 | Form: TABLET
Manufacturer: Chartwell RX, LLC
Category: prescription | Type: HUMAN PRESCRIPTION DRUG LABEL
Date: 20241218

ACTIVE INGREDIENTS: AMOXAPINE 25 mg/1 1
INACTIVE INGREDIENTS: DIBASIC CALCIUM PHOSPHATE DIHYDRATE; MICROCRYSTALLINE CELLULOSE; STARCH, CORN; HYPROMELLOSE, UNSPECIFIED; CROSCARMELLOSE SODIUM; SODIUM STEARYL FUMARATE

Amoxapine Tablets, USP
Rx only

Suicidality and Antidepressant Drugs

Antidepressants increased the risk compared to placebo of suicidal thinking and behavior (suicidality) in children, adolescents, and young adults in short-term studies of major depressive disorder (MDD) and other psychiatric disorders. Anyone considering the use of amoxapine or any other antidepressant in a child, adolescent, or young adult must balance this risk with the clinical need. Short-term studies did not show an increase in the risk of suicidality with antidepressants compared to placebo in adults beyond age 24; there was a reduction in risk with antidepressants compared to placebo in adults aged 65 and older. Depression and certain other psychiatric disorders are themselves associated with increases in the risk of suicide. Patients of all ages who are started on antidepressant therapy should be monitored appropriately and observed closely for clinical worsening, suicidality, or unusual changes in behavior. Families and caregivers should be advised of the need for close observation and communication with the prescriber. Amoxapine is not approved for use in pediatric patients. (See Warnings: Clinical Worsening and Suicide Risk, Precautions: Information for Patients, and Precautions: Pediatric Use)

DESCRIPTION

Amoxapine is an antidepressant of the dibenzoxazepine class, chemically distinct from the dibenzazepines, dibenzocycloheptenes, and dibenzoxepines.

It is designated chemically as 2-Chloro-11-(1-piperazinyl)dibenz[b,f][1,4]oxazepine. The structural formula is represented below:

C17H16CIN3O M.W. 313.78

Amoxapine is supplied for oral administration as 25 mg, 50 mg, 100 mg and 150 mg tablets.

Amoxapine Tablets USP, 25 mg, 50 mg, 100 mg and 150 mg contain: dibasic calcium phosphate dihydrate, microcrystalline cellulose, pregelatinized starch, hypromellose, croscarmellose sodium, and sodium stearyl fumarate.

CLINICAL PHARMACOLOGY

Amoxapine is an antidepressant with a mild sedative component to its action. The mechanism of its clinical action in man is not well understood. In animals, amoxapine reduced the uptake of norepinephrine and serotonin and blocked the response of dopamine receptors to dopamine. Amoxapine is not a monoamine oxidase inhibitor.

Amoxapine is absorbed rapidly and reaches peak blood levels approximately 90 minutes after ingestion. It is almost completely metabolized. The main route of excretion is the kidney. In vitrotests show that amoxapine binding to human serum is approximately 90%.

In man, amoxapine serum concentration declines with a half-life of eight hours. However, the major metabolite, 8-hydroxyamoxapine, has a biologic half-life of 30 hours. Metabolites are excreted in the urine in conjugated form as glucuronides.

Clinical studies have demonstrated that amoxapine has a more rapid onset of action than either amitriptyline or imipramine. The initial clinical effect may occur within four to seven days and occurs within two weeks in over 80% of responders.

INDICATIONS AND USAGE

Amoxapine is indicated for the relief of symptoms of depression in patients with neurotic or reactive depressive disorders as well as endogenous and psychotic depressions. It is indicated for depression accompanied by anxiety or agitation.

CONTRAINDICATIONS

Amoxapine is contraindicated in patients who have shown prior hypersensitivity to dibenzoxazepine compounds. It should not be given concomitantly with monoamine oxidase inhibitors. Hyperpyretic crises, severe convulsions, and deaths have occurred in patients receiving tricyclic antidepressants and monoamine oxidase inhibitors simultaneously. When it is desired to replace a monoamine oxidase inhibitor with amoxapine, a minimum of 14 days should be allowed to elapse after the former is discontinued. Amoxapine should then be initiated cautiously with gradual increase in dosage until optimum response is achieved. The drug is not recommended for use during the acute recovery phase following myocardial infarction.

WARNINGS

Clinical Worsening and Suicide Risk

Patients with major depressive disorder (MDD), both adult and pediatric, may experience worsening of their depression and/or the emergence of suicidal ideation and behavior (suicidality) or unusual changes in behavior, whether or not they are taking antidepressant medications, and this risk may persist until significant remission occurs. Suicide is a known risk of depression and certain other psychiatric disorders, and these disorders themselves are the strongest predictors of suicide. There has been a long-standing concern, however, that antidepressants may have a role in inducing worsening of depression and the emergence of suicidality in certain patients during the early phases of treatment. Pooled analyses of short-term placebo-controlled trials of antidepressant drugs (SSRIs and others) showed that these drugs increase the risk of suicidal thinking and behavior (suicidality) in children, adolescents, and young adults (ages 18-24) with major depressive disorder (MDD) and other psychiatric disorders. Short-term studies did not show an increase in the risk of suicidality with antidepressants compared to placebo in adults beyond age 24; there was a reduction with antidepressants compared to placebo in adults aged 65 and older.

The pooled analyses of placebo-controlled trials in children and adolescents with MDD, obsessive compulsive disorder (OCD), or other psychiatric disorders included a total of 24 short-term trials of 9 antidepressant drugs in over 4400 patients. The pooled analyses of placebo-controlled trials in adults with MDD or other psychiatric disorders included a total of 295 short-term trials (median duration of 2 months) of 11 antidepressant drugs in over 77,000 patients. There was considerable variation in risk of suicidality among drugs, but a tendency toward an increase in the younger patients for almost all drugs studied. There were differences in absolute risk of suicidality across the different indications, with the highest incidence in MDD. The risk differences (drug vs placebo), however, were relatively stable within age strata and across indications. These risk differences (drug-placebo difference in the number of cases of suicidality per 1000 patients treated) are provided in Table 1.

Table 1
Age Range | Drug-Placebo Difference in Number of Cases of Suicidality per 1000 Patients Treated
 | Increases Compared to Placebo
<18 | 14 additional cases
18-24 | 5 additional cases
 | Decreases Compared to Placebo
25-64 | 1 fewer case
≥65 | 6 fewer cases

No suicides occurred in any of the pediatric trials. There were suicides in the adult trials, but the number was not sufficient to reach any conclusion about drug effect on suicide.

It is unknown whether the suicidality risk extends to longer-term use, i.e., beyond several months. However, there is substantial evidence from placebo-controlled maintenance trials in adults with depression that the use of antidepressants can delay the recurrence of depression.

All patients being treated with antidepressants for any indication should be monitored appropriately and observed closely for clinical worsening, suicidality, and unusual changes in behavior, especially during the initial few months of a course of drug therapy, or at times of dose changes, either increases or decreases.

The following symptoms, anxiety, agitation, panic attacks, insomnia, irritability, hostility, aggressiveness, impulsivity, akathisia (psychomotor restlessness), hypomania, and mania, have been reported in adult and pediatric patients being treated with antidepressants for major depressive disorder as well as for other indications, both psychiatric and nonpsychiatric. Although a causal link between the emergence of such symptoms and either the worsening of depression and/or the emergence of suicidal impulses has not been established, there is concern that such symptoms may represent precursors to emerging suicidality.

Consideration should be given to changing the therapeutic regimen, including possibly discontinuing the medication, in patients whose depression is persistently worse, or who are experiencing emergent suicidality or symptoms that might be precursors to worsening depression or suicidality, especially if these symptoms are severe, abrupt in onset, or were not part of the patient's presenting symptoms.

Families and caregivers of patients being treated with antidepressants for major depressive disorder or other indications, both psychiatric and nonpsychiatric, should be alerted about the need to monitor patients for the emergence of agitation, irritability, unusual changes in behavior, and the other symptoms described above, as well as the emergence of suicidality, and to report such symptoms immediately to health care providers. Such monitoring should include daily observation by families and caregivers.Prescriptions for amoxapine should be written for the smallest quantity of tablets consistent with good patient management, in order to reduce the risk of overdose.

Screening Patients for Bipolar Disorder:A major depressive episode may be the initial presentation of bipolar disorder. It is generally believed (though not established in controlled trials) that treating such an episode with an antidepressant alone may increase the likelihood of precipitation of a mixed/manic episode in patients at risk for bipolar disorder. Whether any of the symptoms described above represent such a conversion is unknown. However, prior to initiating treatment with an antidepressant, patients with depressive symptoms should be adequately screened to determine if they are at risk for bipolar disorder; such screening should include a detailed psychiatric history, including a family history of suicide, bipolar disorder, and depression. It should be noted that amoxapine is not approved for use in treating bipolar depression.

Angle-Closure Glaucoma

The pupillary dilation that occurs following use of many antidepressant drugs including amoxapine, may trigger an angle closure attack in a patient with anatomically narrow angles who does not have a patent iridectomy.

Tardive Dyskinesia

Tardive dyskinesia, a syndrome consisting of potentially irreversible, involuntary, dyskinetic movements may develop in patients treated with neuroleptic (i.e., antipsychotic) drugs. (Amoxapine is not an antipsychotic, but it has substantive neuroleptic activity.) Although the prevalence of the syndrome appears to be highest among the elderly, especially elderly women, it is impossible to rely upon prevalence estimates to predict, at the inception of neuroleptic treatment, which patients are likely to develop the syndrome. Whether neuroleptic drug products differ in their potential to cause tardive dyskinesia is unknown.

Both the risk of developing the syndrome and the likelihood that it will become irreversible are believed to increase as the duration of treatment and the total cumulative dose of neuroleptic drugs administered to the patient increase. However, the syndrome can develop, although much less commonly, after relatively brief treatment periods at low doses.

There is no known treatment for established cases of tardive dyskinesia, although the syndrome may remit, partially or completely, if neuroleptic treatment is withdrawn. Neuroleptic treatment itself, however, may suppress (or partially suppress) the signs and symptoms of the syndrome and thereby may possibly mask the underlying disease process. The effect that symptomatic suppression has upon the long-term course of the syndrome is unknown.

Given these considerations, neuroleptics should be prescribed in a manner that is most likely to minimize the occurrence of tardive dyskinesia. Chronic neuroleptic treatment should generally be reserved for patients who suffer from a chronic illness that, 1) is known to respond to neuroleptic drugs, and, 2) for whom alternative, equally effective, but potentially less harmful treatments are not available or appropriate. In patients who do require chronic treatment, the smallest dose and the shortest duration of treatment producing a satisfactory clinical response should be sought. The need for continued treatment should be reassessed periodically.

If signs and symptoms of tardive dyskinesia appear in a patient on neuroleptics, drug discontinuation should be considered. However, some patients may require treatment despite the presence of the syndrome.

(For further information about the description of tardive dyskinesia and its clinical detection, please refer to the sections on Information for Patients and ADVERSE REACTIONS.)

Neuroleptic Malignant Syndrome (NMS)

A potentially fatal symptom complex sometimes referred to as Neuroleptic Malignant Syndrome (NMS) has been reported in association with antipsychotic drugs and with amoxapine. Clinical manifestations of NMS are hyperpyrexia, muscle rigidity, altered mental status and evidence of autonomic instability (irregular pulse or blood pressure, tachycardia, diaphoresis, and cardiac dysrhythmias).

The diagnostic evaluation of patients with this syndrome is complicated. In arriving at a diagnosis, it is important to identify cases where the clinical presentation includes both serious medical illness (e.g., pneumonia, systemic infection, etc.) and untreated or inadequately treated extrapyramidal signs and symptoms (EPS). Other important considerations in the differential diagnosis include central anticholinergic toxicity, heat stroke, drug fever and primary central nervous system (CNS) pathology.

The management of NMS should include 1) immediate discontinuation of antipsychotic drugs and other drugs not essential to concurrent therapy, 2) intensive symptomatic treatment and medical monitoring, and 3) treatment of any concomitant serious medical problems for which specific treatments are available. There is no general agreement about specific pharmacological treatment regimens for uncomplicated NMS.

If a patient requires antipsychotic drug treatment after recovery from NMS, the potential reintroduction of drug therapy should be carefully considered. The patient should be carefully monitored since recurrences of NMS have been reported.

Amoxapine should be used with caution in patients with a history of urinary retention, angle closure glaucoma, or increased intraocular pressure. Patients with cardiovascular disorders should be watched closely. Tricyclic antidepressant drugs, particularly when given in high doses, can induce sinus tachycardia, changes in conduction time, and arrhythmias. Myocardial infarction and stroke have been reported with drugs of this class.

Extreme caution should be used in treating patients with a history of convulsive disorder or those with overt or latent seizure disorders.

PRECAUTIONS

General

In prescribing the drug it should be borne in mind that the possibility of suicide is inherent in any severe depression, and persists until a significant remission occurs; the drug should be dispensed in the smallest suitable amount. Manic depressive patients may experience a shift to the manic phase. Schizophrenic patients may develop increased symptoms of psychosis; patients with paranoid symptomatology may have an exaggeration of such symptoms. This may require reduction of dosage or the addition of a major tranquilizer to the therapeutic regimen. Antidepressant drugs can cause skin rashes and/or “drug fever” in susceptible individuals. These allergic reactions may, in rare cases, be severe. They are more likely to occur during the first few days of treatment, but may also occur later. Amoxapine should be discontinued if rash and/or fever develop. Amoxapine possesses a degree of dopamine-blocking activity which may cause extrapyramidal symptoms in <1% of patients. Rarely, symptoms indicative of tardive dyskinesia have been reported.

Information for Patients

Given the likelihood that some patients exposed chronically to neuroleptics will develop tardive dyskinesia, it is advised that all patients in whom chronic use is contemplated be given, if possible, full information about this risk. The decision to inform patients and/or their guardians must obviously take into account the clinical circumstances and the competency of the patient to understand the information provided.

Patients should be warned of the possibility of drowsiness that may impair performance of potentially hazardous tasks such as driving an automobile or operating machinery.

Prescribers or other health professionals should inform patients, their families, and their caregivers about the benefits and risks associated with treatment with amoxapine and should counsel them in its appropriate use. A patient Medication Guide about “Antidepressant Medicines, Depression and other Serious Mental Illness, and Suicidal Thoughts or Actions” is available for amoxapine. The prescriber or health professional should instruct patients, their families, and their caregivers to read the Medication Guide and should assist them in understanding its contents. Patients should be given the opportunity to discuss the contents of the Medication Guide and to obtain answers to any questions they may have. The complete text of the Medication Guide is reprinted at the end of this document.

Patients should be advised of the following issues and asked to alert their prescriber if these occur while taking amoxapine.

Patients should be advised that taking amoxapine can cause mild pupillary dilation, which in susceptible individuals, can lead to an episode of angle-closure glaucoma. Pre-existing glaucoma is almost always open-angle glaucoma because angle-closure glaucoma, when diagnosed, can be treated definitively with iridectomy. Open-angle glaucoma is not a risk factor for angle closure glaucoma. Patients may wish to be examined to determine whether they are susceptible to angle closure, and have a prophylactic procedure (e.g., iridectomy), if they are susceptible.

Clinical Worsening and Suicide Risk:Patients, their families, and their caregivers should be encouraged to be alert to the emergence of anxiety, agitation, panic attacks, insomnia, irritability, hostility, aggressiveness, impulsivity, akathisia (psychomotor restlessness), hypomania, mania, other unusual changes in behavior, worsening of depression, and suicidal ideation, especially early during antidepressant treatment and when the dose is adjusted up or down. Families and caregivers of patients should be advised to look for the emergence of such symptoms on a day-to-day basis, since changes may be abrupt. Such symptoms should be reported to the patient's prescriber or health professional, especially if they are severe, abrupt in onset, or were not part of the patient's presenting symptoms. Symptoms such as these may be associated with an increased risk for suicidal thinking and behavior and indicate a need for very close monitoring and possibly changes in the medication.

Drug Interactions

See CONTRAINDICATIONSabout concurrent usage of tricyclic antidepressants and monoamine oxidase inhibitors. Paralytic ileus may occur in patients taking tricyclic antidepressants in combination with anticholinergic drugs. Amoxapine may enhance the response to alcohol and the effects of barbiturates and other CNS depressants. Serum levels of several tricyclic antidepressants have been reported to be significantly increased when cimetidine is administered concurrently. Although such an interaction has not been reported to date with amoxapine, specific interaction studies have not been done, and the possibility should be considered.

Drugs Metabolized by P450 2D6

The biochemical activity of the drug metabolizing isozyme cytochrome P450 2D6 (debrisoquin hydroxylase) is reduced in a subset of the caucasian population (about 7 to 10% of caucasians are so called “poor metabolizers”); reliable estimates of the prevalence of reduced P450 2D6 isozyme activity among Asian, African and other populations are not yet available. Poor metabolizers have higher than expected plasma concentrations of tricyclic antidepressants (TCAs) when given usual doses. Depending on the fraction of drug metabolized by P450 2D6, the increase in plasma concentration may be small, or quite large (8 fold increase in plasma AUC of the TCA).

In addition, certain drugs inhibit the activity of this isozyme and make normal metabolizers resemble poor metabolizers. An individual who is stable on a given dose of TCA may become abruptly toxic when given one of these inhibiting drugs as concomitant therapy. The drugs that inhibit cytochrome P450 2D6 include some that are not metabolized by the enzyme (quinidine, cimetidine) and many that are substrates for P450 2D6 (many other antidepressants, phenothiazines, and the Type 1C antiarrhythmics propafenone and flecainide). While all the selective serotonin reuptake inhibitors (SSRIs), e.g., fluoxetine, sertraline, and paroxetine, inhibit P450 2D6, they may vary in the extent of inhibition. The extent to which SSRI-TCA interactions may pose clinical problems will depend on the degree of inhibition and the pharmacokinetics of the SSRI involved. Nevertheless, caution is indicated in the co-administration of TCAs with any of the SSRIs and also in switching from one class to the other. Of particular importance, sufficient time must elapse before initiating TCA treatment in a patient being withdrawn from fluoxetine, given the long half-life of the parent and active metabolite (at least 5 weeks may be necessary).

Concomitant use of tricyclic antidepressants with drugs that can inhibit cytochrome P450 2D6 may require lower doses than usually prescribed for either the tricyclic antidepressant or the other drug. Furthermore, whenever one of these other drugs is withdrawn from co-therapy, an increased dose of tricyclic antidepressant may be required. It is desirable to monitor TCA plasma levels whenever a TCA is going to be co-administered with another drug known to be an inhibitor of P450 2D6.

Therapeutic Interactions

Concurrent administration with electroshock therapy may increase the hazards associated with such therapy.

Carcinogenesis, Impairment of Fertility

In a 21-month toxicity study at three dose levels in rats, pancreatic islet cell hyperplasia occurred with slightly increased incidence at doses 5-10 times the human dose. Pancreatic adenocarcinoma was detected in low incidence in the mid-dose group only, and may possibly have resulted from endocrine-mediated organ hyperfunction. The significance of these findings to man is not known.

Treatment of male rats with 5-10 times the human dose resulted in a slight decrease in the number of fertile matings. Female rats receiving oral doses within the therapeutic range displayed a reversible increase in estrous cycle length.

Pregnancy

Pregnancy Category C

Studies performed in mice, rats, and rabbits have demonstrated no evidence of teratogenic effect due to amoxapine. Embryotoxicity was seen in rats and rabbits given oral doses approximating the human dose. Fetotoxic effects (intrauterine death, stillbirth, decreased birth weight) were seen in animals studied at oral doses 3-10 times the human dose. Decreased postnatal survival (between days 0-4) was demonstrated in the offspring of rats at 5-10 times the human dose. There are no adequate and well-controlled studies in pregnant women. Amoxapine should be used during pregnancy only if the potential benefit justifies the potential risk to the fetus.

Nursing Mothers

Amoxapine, like many other systemic drugs, is excreted in human milk. Because effects of the drug on infants are unknown, caution should be exercised when amoxapine is administered to nursing women.

Pediatric Use

Safety and effectiveness in the pediatric population have not been established (see BOX WARNINGand WARNINGS– Clinical Worsening and Suicide Risk).

Anyone considering the use of amoxapine in a child or adolescent must balance the potential risks with the clinical need.

Geriatric Use

Clinical studies of amoxapine were not adequate to determine whether subjects aged 65 and over respond differently from younger subjects.

Amoxapine is known to be substantially excreted by the kidney (see CLINICAL PHARMACOLOGY). Clinical circumstances, some of which may be more common in the elderly, such as hepatic or renal impairment, should be considered.

Greater sensitivity (e.g., tardive dyskinesia, sedation) of some older individuals cannot be ruled out (see WARNINGSand ADVERSE REACTIONS). In general, dose selection for an elderly patient should be cautious, usually starting at a lower dose (see DOSAGE AND ADMINISTRATION).

ADVERSE REACTIONS

Adverse reactions reported in controlled studies in the United States are categorized with respect to incidence below. Following this is a listing of reactions known to occur with other antidepressant drugs of this class.

Incidence Greater Than 1%

The most frequent types of adverse reactions occurring with amoxapine in controlled clinical trials were sedative and anticholinergic: these included drowsiness (14%), dry mouth (14%), constipation (12%), and blurred vision (7%).

Less frequently reported reactions are:

CNS and Neuromuscular:anxiety, insomnia, restlessness, nervousness, palpitations, tremors, confusion, excitement, nightmares, ataxia, alterations in EEG patterns.

Allergic:edema, skin rash.

Endocrine:elevation of prolactin levels.

Gastrointestinal:nausea.

Other:dizziness, headache, fatigue, weakness, excessive appetite, increased perspiration.

Incidence Less Than 1%

Anticholinergic:disturbances of accommodation, mydriasis, delayed micturition, urinary retention, nasal stuffiness.

Cardiovascular:hypotension, hypertension, syncope, tachycardia.

Allergic:drug fever, urticaria, photosensitization, pruritus, vasculitis, hepatitis.

CNS and Neuromuscular:tingling, paresthesias of the extremities, tinnitus, disorientation, seizures, hypomania, numbness, incoordination, disturbed concentration, hyperthermia, extrapyramidal symptoms, including, tardive dyskinesia. Neuroleptic malignant syndrome has been reported. (See WARNINGS.)

Hematologic:leukopenia, agranulocytosis.

Gastrointestinal:epigastric distress, vomiting, flatulence, abdominal pain, peculiar taste, diarrhea.

Endocrine:increased or decreased libido, impotence, menstrual irregularity, breast enlargement and galactorrhea in the female, syndrome of inappropriate antidiuretic hormone secretion.

Other:lacrimation, weight gain or loss, altered liver function, painful ejaculation.

Drug Relationship Unknown

The following reactions have been reported rarely, and occurred under uncontrolled circumstances where a drug relationship was difficult to assess. These observations are listed to serve as alerting information to physicians.

Anticholinergic:paralytic ileus.

Cardiovascular:atrial arrhythmias (including atrial fibrillation), myocardial infarction, stroke, heart block.

CNS and Neuromuscular:hallucinations.

Hematologic:thrombocytopenia, eosinophilia, purpura, petechiae.

Gastrointestinal:parotid swelling.

Endocrine:change in blood glucose levels.

Other:pancreatitis, hepatitis, jaundice, urinary frequency, testicular swelling, anorexia, alopecia.

Additional Adverse Reactions

The following reactions have been reported with other antidepressant drugs.

Anticholinergic:sublingual adenitis, dilation of the urinary tract.

CNS and Neuromuscular:delusions.

Gastrointestinal:stomatitis, black tongue.

Endocrine:gynecomastia.

To report SUSPECTED ADVERSE EVENTS, contact Chartwell RX, LLC. at 1-845-232-1683 or FDA at 1-800-FDA-100 or http://www.fda.gov/for voluntary reporting of adverse reactions.

OVERDOSAGE

Signs and Symptoms

Toxic manifestations of amoxapine overdosage differ significantly from those of other tricyclic antidepressants. Serious cardiovascular effects are seldom if ever observed. However, CNS effects - particularly grand mal convulsions - occur frequently, and treatment should be directed primarily toward prevention or control of seizures. Status epilepticus may develop and constitutes a neurologic emergency. Coma and acidosis are other serious complications of substantial amoxapine overdosage in some cases. Fatal overdoses with amoxapine have occurred.

Renal failure may develop two to five days after toxic overdosage in patients who may appear otherwise recovered. Acute tubular necrosis with rhabdomyolysis and myoglobinuria is the most common renal complication in such cases. This reaction probably occurs in less than 5% of overdose cases, and typically in those who have experienced multiple seizures.

Treatment

Treatment of amoxapine overdosage should be symptomatic and supportive, but with special attention to prevention or control of seizures. If the patient is conscious, induced emesis followed by gastric lavage with appropriate precautions to prevent pulmonary aspiration should be accomplished as soon as possible. Following lavage, activated charcoal may be administered to reduce absorption, and repeated administrations may facilitate drug elimination. An adequate airway should be established in comatose patients and assisted ventilation instituted if necessary. Seizures may respond to standard anticonvulsant therapy such as intravenous diazepam and/or phenytoin. The value of physostigmine appears less certain. Status epilepticus, should it develop, requires vigorous treatment such as that described by Delgado-Escueta et al (N Engl J Med1982; 306:1337-1340).

Convulsions, when they occur, typically begin within 12 hours after ingestion. Because seizures may occur precipitously in some overdosage patients who appear otherwise relatively asymptomatic, the treating physician may wish to consider prophylactic administration of anticonvulsant medication during this period.

Treatment of renal impairment, should it occur, is the same as that for nondrug-induced renal dysfunction.

Serious cardiovascular effects are rare following amoxapine overdosage, and the ECG typically remains within normal limits except for sinus tachycardia. Hence, prolongation of the QRS interval beyond 100 milliseconds within the first 24 hours is nota useful guide to the severity of overdosage with this drug.

Fatalities and neurologic sequelae have resulted from prolonged status epilepticus in amoxapine overdosage patients. While the lethal dose appears higher than that of other tricyclic antidepressants (80% of lethal amoxapine overdosages have involved ingestion of 3 grams or more), many factors other than amount ingested are important in assessing probability of survival. These include age and physical condition of the patient, concomitant ingestion of other drugs, and especially the interval between drug ingestion and initiation of emergency treatment.

DOSAGE AND ADMINISTRATION

Effective dosage of amoxapine may vary from one patient to another. Usual effective dosage is 200 to 300 mg daily. Three weeks constitutes an adequate period of trial providing dosage has reached 300 mg daily (or lower level of tolerance) for at least two weeks. If no response is seen at 300 mg, dosage may be increased, depending upon tolerance, up to 400 mg daily. Hospitalized patients who have been refractory to antidepressant therapy and who have no history of convulsive seizures may have dosage raised cautiously up to 600 mg daily in divided doses.

Amoxapine may be given in a single daily dose, not to exceed 300 mg, preferably at bedtime. If the total daily dosage exceeds 300 mg, it should be given in divided doses.

Initial Dosage for Adults

Usual starting dosage is 50 mg two or three times daily. Depending upon tolerance, dosage may be increased to 100 mg two or three times daily by the end of the first week. (Initial dosage of 300 mg daily may be given, but notable sedation may occur in some patients during the first few days of therapy at this level.) Increases above 300 mg daily should be made only if 300 mg daily has been ineffective during a trial period of at least two weeks. When effective dosage is established, the drug may be given in a single dose (not to exceed 300 mg) at bedtime.

Elderly Patients

In general, lower dosages are recommended for these patients. Recommended starting dosage of amoxapine is 25 mg two or three times daily. If no intolerance is observed, dosage may be increased by the end of the first week to 50 mg two or three times daily. Although 100 to 150 mg daily may be adequate for many elderly patients, some may require higher dosage. Careful increases up to 300 mg daily are indicated in such cases.

Once an effective dosage is established, amoxapine may conveniently be given in a single bedtime dose, not to exceed 300 mg.

Maintenance

Recommended maintenance dosage of amoxapine is the lowest dose that will maintain remission. If symptoms reappear, dosage should be increased to the earlier level until they are controlled.

For maintenance therapy at dosages of 300 mg or less, a single dose at bedtime is recommended.

HOW SUPPLIED

Amoxapine tablets, USP for oral administration are available as:

25 mg:White to off white, round, scored tablets, debossed ‘CE’ above the bisect and ‘166’ on one side and plain on the other side.

NDC 62135-700-90 in bottles of 90 tablets

50 mg:White to off white, round, scored tablets, debossed ‘CE’ above the bisect and ‘167’ on one side and plain on the other side.

NDC 62135-701-90 in bottles of 90 tablets

100 mg:White to off white, round, scored tablets, debossed ‘CE’ above the bisect and ‘168’ on one side and plain on the other side.

NDC 62135-702-90 in bottles of 90 tablets

150 mg:White to off white, round, scored tablets, debossed ‘CE’ above the bisect and ‘169’ on one side and plain on the other side.

NDC 62135-703-30 in bottles of 30 tablets

Dispense in a tight container with child-resistant closure.

Store at 20-25°C (68-77°F). [See USP Controlled Room Temperature.]

Manufactured for:
Chartwell RX, LLC.
Congers, NY 10920

L71686

Revised 09/2023-01

Print Medication Guides at: www.chartwellpharma.com/medguides

Medication Guide

Antidepressant Medicines, Depression and other Serious Mental Illnesses, and Suicidal Thoughts or Actions

Read the Medication Guide that comes with you or your family member’s antidepressant medicine. This Medication Guide is only about the risk of suicidal thoughts and actions with antidepressant medicines. Talk to your, or your family member’s, healthcare provider about:

- all risks and benefits of treatment with antidepressant medicines
- all treatment choices for depression or other serious mental illness

What is the most important information I should know about antidepressant medicines, depression and other serious mental illnesses, and suicidal thoughts or actions?

1. Antidepressant medicines may increase suicidal thoughts or actions in some children, teenagers, and young adults within the first few months of treatment.

2. Depression and other serious mental illnesses are the most important causes of suicidal thoughts and actions. Some people may have a particularly high risk of having suicidal thoughts or actions.These include people who have (or have a family history of) bipolar illness (also called manic-depressive illness) or suicidal thoughts or actions.

3. How can I watch for and try to prevent suicidal thoughts and actions in myself or a family member?

- Pay close attention to any changes, especially sudden changes, in mood, behaviors, thoughts, or feelings. This is very important when an antidepressant medicine is started or when the dose is changed.

- Call the healthcare provider right away to report new or sudden changes in mood, behavior, thoughts, or feelings.

- Keep all follow-up visits with the healthcare provider as scheduled. Call the healthcare provider between visits as needed, especially if you have concerns about symptoms.

Call a healthcare provider right away if you or your family member has any of the following symptoms, especially if they are new, worse, or worry you:

- thoughts about suicide or dying
- attempts to commit suicide
- new or worse depression
- new or worse anxiety
- feeling very agitated or restless
- panic attacks
- trouble sleeping (insomnia)
- new or worse irritability
- acting aggressive, being angry, or violent
- acting on dangerous impulses
- an extreme increase in activity and talking (mania)
- other unusual changes in behavior or Mood
- Visual problems:eye pain, changes in vision, swelling or redness in or around the eye

What else do I need to know about antidepressant medicines?

- Never stop an antidepressant medicine without first talking to a healthcare provider.Stopping an antidepressant medicine suddenly can cause other symptoms.
- Visual problems:Only some people are at risk for these problems. You may want to undergo an eye examination to see if you are at risk and receive preventative treatment if you are.
- Antidepressants are medicines used to treat depression and other illnesses.It is important to discuss all the risks of treating depression and also the risks of not treating it. Patients and their families or other caregivers should discuss all treatment choices with the healthcare provider, not just the use of antidepressants.
- Antidepressant medicines have other side effects.Talk to the healthcare provider about the side effects of the medicine prescribed for you or your family member.
- Antidepressant medicines can interact with other medicines.Know all of the medicines that you or your family member takes. Keep a list of all medicines to show the healthcare provider. Do not start new medicines without first checking with your healthcare provider.
- Not all antidepressant medicines prescribed for children are FDA approved for use in children.Talk to your child’s healthcare provider for more information.

Call your doctor for medical advice about side effects. You may report side effects to FDA at 1-800-FDA-1088.

This Medication Guide has been approved by the U.S. Food and Drug Administration for all antidepressants.

Manufactured for:
Chartwell RX, LLC.
Congers, NY 10920

L71687

Revised 09/2023-01

PACKAGE LABEL

Amoxapine Tablets, USP 25mg- NDC 62135-700-90 -90s Bottle Label

Amoxapine Tablets, USP 50mg- NDC 62135-701-90 -90s Bottle Label

Amoxapine Tablets, USP 100mg- NDC 62135-702-90 -90s Bottle Label

Amoxapine Tablets, USP 150mg- NDC 62135-703-30 -30s Bottle Label